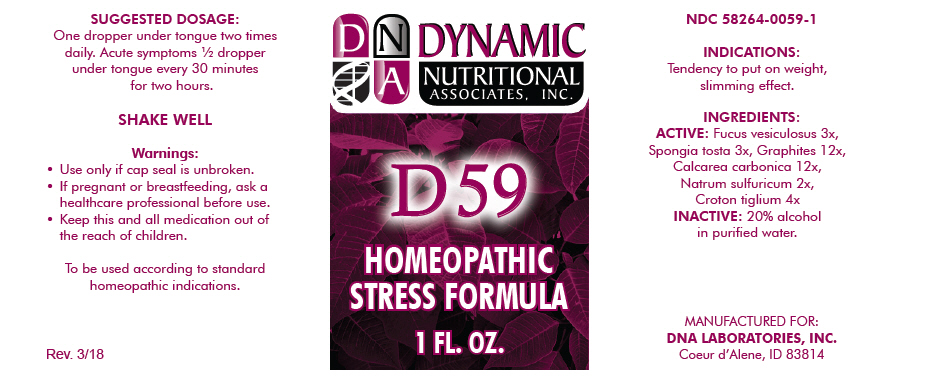 DRUG LABEL: D-59
NDC: 58264-0059 | Form: SOLUTION
Manufacturer: DNA Labs, Inc.
Category: homeopathic | Type: HUMAN OTC DRUG LABEL
Date: 20250113

ACTIVE INGREDIENTS: FUCUS VESICULOSUS 3 [hp_X]/1 mL; SPONGIA OFFICINALIS SKELETON, ROASTED 3 [hp_X]/1 mL; GRAPHITE 12 [hp_X]/1 mL; OYSTER SHELL CALCIUM CARBONATE, CRUDE 12 [hp_X]/1 mL; SODIUM SULFATE 2 [hp_X]/1 mL; CROTON OIL 4 [hp_X]/1 mL
INACTIVE INGREDIENTS: ALCOHOL; WATER

D-59

NDC 58264-0059-1

INDICATIONS

PURPOSE

Tendency to put on weight, slimming effect.

INGREDIENTS

ACTIVE

Fucus vesiculosus 3x, Spongia tosta 3x, Graphites 12x, Calcarea carbonica 12x, Natrum sulfuricum 2x, Croton tiglium 4x

INACTIVE

20% alcohol in purified water.

SUGGESTED DOSAGE

One dropper under tongue two times daily. Acute symptoms ½ dropper under tongue every 30 minutes for two hours.

STORAGE AND HANDLING

SHAKE WELL

Warnings

- Use only if cap seal is unbroken.

PREGNANCY OR BREAST FEEDING

- If pregnant or breastfeeding, ask a healthcare professional before use.

KEEP OUT OF REACH OF CHILDREN

- Keep this and all medication out of the reach of children.

To be used according to standard homeopathic indications.

PRINCIPAL DISPLAY PANEL - 1 FL. OZ. Bottle Label

DYNAMIC
NUTRITIONAL
ASSOCIATES, INC.

D 59

HOMEOPATHIC
STRESS FORMULA

1 FL. OZ.